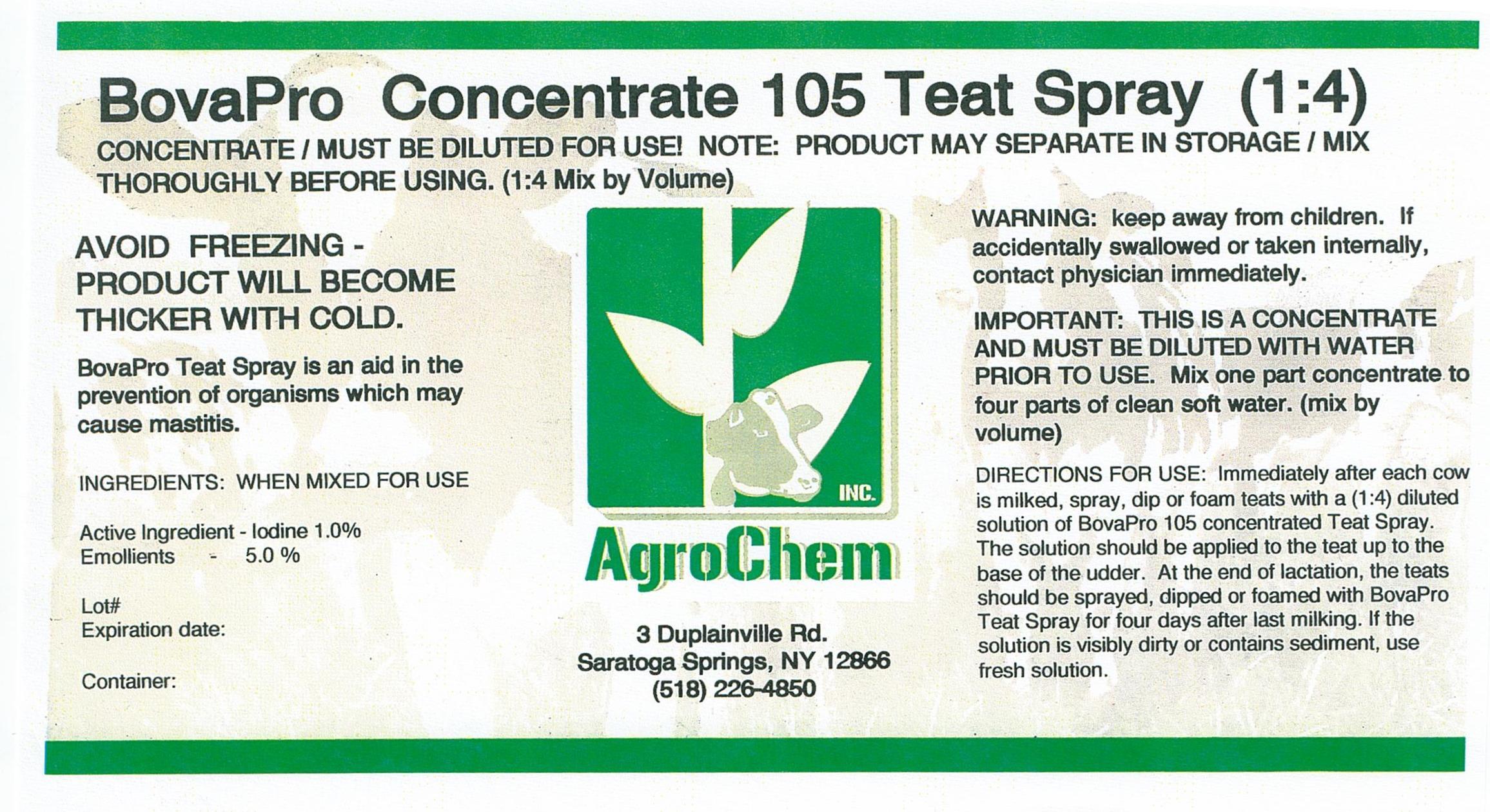 DRUG LABEL: Bova Pro 105 
NDC: 17307-1051 | Form: SPRAY
Manufacturer: AgroChem Inc
Category: animal | Type: OTC ANIMAL DRUG LABEL
Date: 20130820

ACTIVE INGREDIENTS: IODINE .01 kg/1 kg
INACTIVE INGREDIENTS: GLYCERIN .025 kg/1 kg; PROPYLENE GLYCOL .025 kg/1 kg; WATER .025 kg/1 kg

Bova Pro 105 Spray Concentrate

PRECAUTIONS

CONCENTRATE/MUST BE DILUTED FOR USE! NOTE: PRODUCT MAY SEPARATE IN STORAGE/

MIX THOROUGHLY BEFORE USING. (1:4 Mix by Volume)

AVOID FREEZING -

PRODUCT WILL BECOME

THICKER WITH COLD

DESCRIPTION

BovaPro Teat Spray is an aid in the

prevention of organisms which may

cause mastitis.

ACTIVE INGREDIENT

INGREDIENTS: WHEN MIXED FOR USE

Active Ingredient - Iodine 1.0%

Emollients - 5.0%

WARNINGS

WARNING: keep away from children. If

accidentally swallowed or taken

internally, contact physician

immediately.

IMPORTANT: THIS IS A CONCENTRATE

AND MUST BE DILUTED WITH WATER

PRIOR TO USE. Mix one part concentrate to

four parts of clean soft water. (mix by

volume)

DIRECTIONS FOR USE: Immediately after each cow

is milked, spray, dip or foam teats with a (1:4) diluted

solution of BovaPro 105 concentrated Teat Spray.

The solution should be applied to the teat up to the

base of the udder. At the end of lactation, the teats

should be sprayed, dipped or foamed with BovaPro

Teat Spray for four days after last milking. If the

solution is visibly dirty or contains sediment, use fresh

solution.